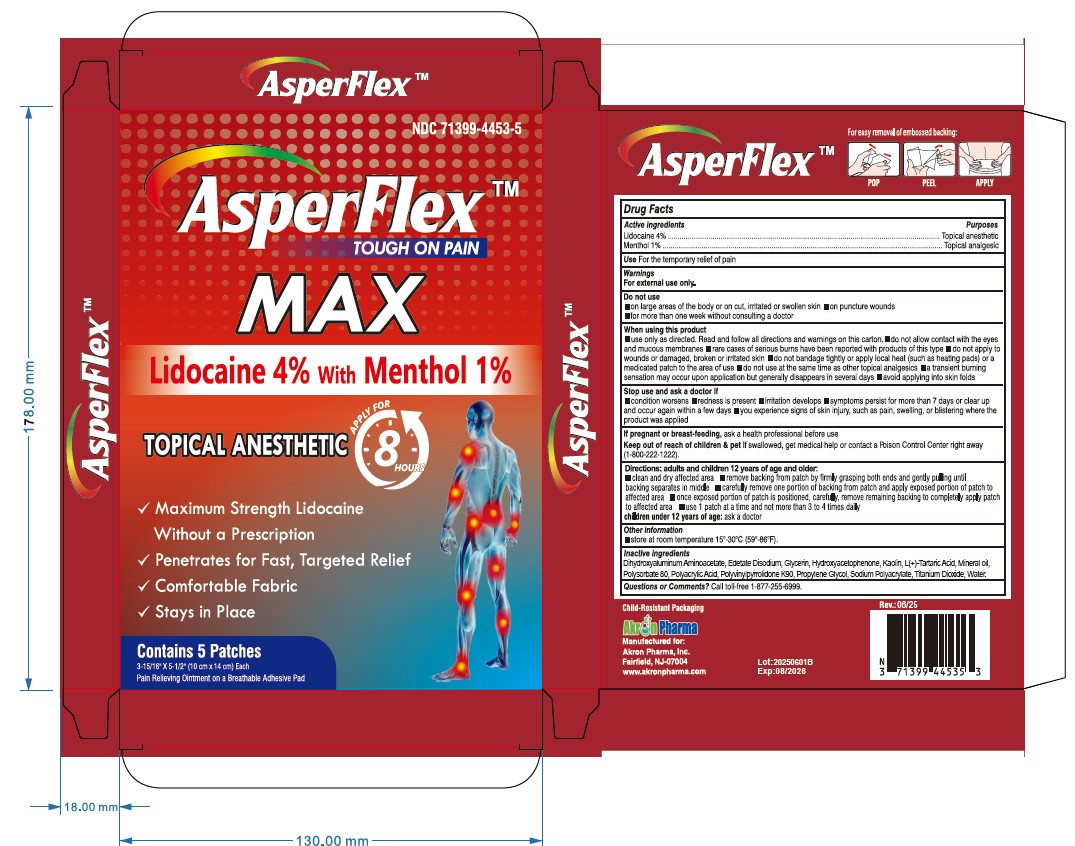 DRUG LABEL: AsperFlex MAX
NDC: 71399-4453 | Form: PATCH
Manufacturer: Akron Pharma Inc.
Category: otc | Type: HUMAN OTC DRUG LABEL
Date: 20250702

ACTIVE INGREDIENTS: LIDOCAINE 240 mg/1 1; MENTHOL 60 mg/1 1
INACTIVE INGREDIENTS: MINERAL OIL; DIHYDROXYALUMINUM AMINOACETATE ANHYDROUS; GLYCERIN; EDETATE DISODIUM; POLYACRYLIC ACID (8000 MW); POLYSORBATE 80; PROPYLENE GLYCOL; SODIUM POLYACRYLATE (8000 MW); HYDROXYACETOPHENONE; TITANIUM DIOXIDE; KAOLIN; TARTARIC ACID; WATER; POVIDONE K90

AsperFlex MAX
Tough on Pain
Lidocaine Patch 4% with Menthol 1%

Active Ingredient

Lidocaine 4%

Menthol 1%

Purpose

Topical anesthetic

Uses

for the temporary relief of pain

Warnings

For external use only

Do not use

- on puncture wounds, cuts, irritated or swollen skin
- more than 1 patch on your body at a time or with other topical analgesics at the same time
- with a heating pad or apply local heat to the area of use

When using this product

- use only as directed. Read and follow all directions and warnings on this carton.
- do not allow contact with the eyes
- do not bandage tightly or apply local heat (such as heating pads) to the area of use
- do not use at the same time as other topical analgesics
- dispose of used patch in manner that always keeps product away from children and pets.Used patches still contain the drug product that can produce serious adverse effects if a child or pet chews oringests this patch

Stop use and ask a doctor if

- condition worsens or symptoms persist for more than 7 days
- symptoms clear up and occur again within a few days
- redness or irritation develops
- you experience signs of skin injury, such as pain, swelling, or blistering where the product was applied

If pregnant or breast-feeding,

ask a health professional before use.

Keep out of reach of childrenand pets.

If swallowed, get medical help or contact a Poison Control Center right away (1-800-222-1222).

Directions

adults and children over 12 years:

- clean and dry affected area
- remove backing from patch by firmly grasping both ends and gently pulling until backing separates in middle
- carefully remove smaller portion of backing from patch and apply exposed portion of patch to affected area
- once exposed portion of patch is positioned, carefully remove remaining backing to completely apply patch to affected area
- use 1 patch at a time and not more than 3 to 4 times daily

children 12 years or younger:consult a doctor

Other Information

store at room temperature 15°-30°C (59°-86°F).

Inactive ingredients

aluminum glycinate, glycerin, methyl acrylate, polyacrylic acid, polysorbate 80, propylene glycol, sodium polyacrylate, tartaric acid, titanium dioxide urea, poval, alcohol, water

Questions or Comments?

Call toll-free 1-877-255-6999.

Manufactured for:

Akron Pharma Inc.,

Fairfield, NJ-07004

www.akronpharma.com